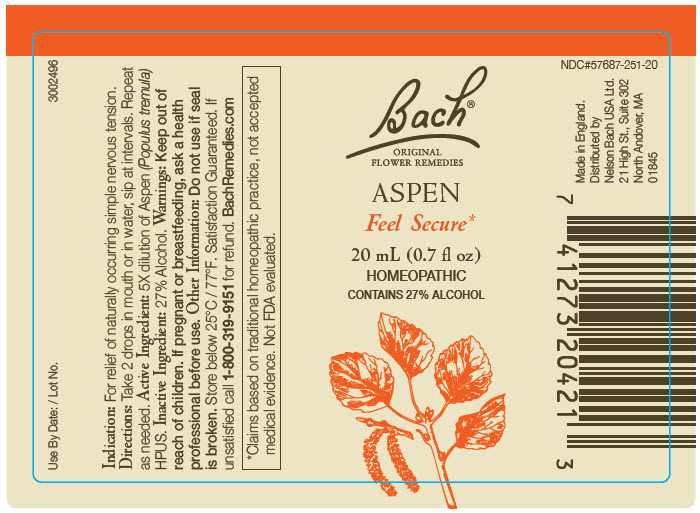 DRUG LABEL: Bach Original Flower Remedies
NDC: 57687-251 | Form: SOLUTION
Manufacturer: Nelson Bach USA Limited
Category: homeopathic | Type: HUMAN OTC DRUG LABEL
Date: 20200514

ACTIVE INGREDIENTS: Populus Tremula Whole 5 [hp_X]/0.095 mL
INACTIVE INGREDIENTS: Alcohol

Bach® Original Flower Remedies

Indication

PURPOSE

For relief of naturally occurring simple nervous tension.

Directions

Take 2 drops in mouth or in water, sip at intervals. Repeat as needed.

Active Ingredient

5X dilution of Aspen (Populus tremula) HPUS.

Inactive Ingredient

27% Alcohol.

Warnings

Keep out of reach of children.

PREGNANCY OR BREAST FEEDING

If pregnant or breastfeeding, ask a health professional before use.

Other Information

Do not use if seal is broken. Store below 25°C / 77℉.

QUESTIONS

Satisfaction Guaranteed. If unsatisfied call 1-800-319-9151 for refund. BachRemedies.com

Distributed by
Nelson Bach USA Ltd.
21 High St., Suite 302
North Andover, MA
01845

PRINCIPAL DISPLAY PANEL - 20 mL Bottle Label

Bach®
ORIGINAL
FLOWER REMEDIES

ASPEN

Feel Secure*

20 mL (0.7 fl oz)
HOMEOPATHIC
CONTAINS 27% ALCOHOL